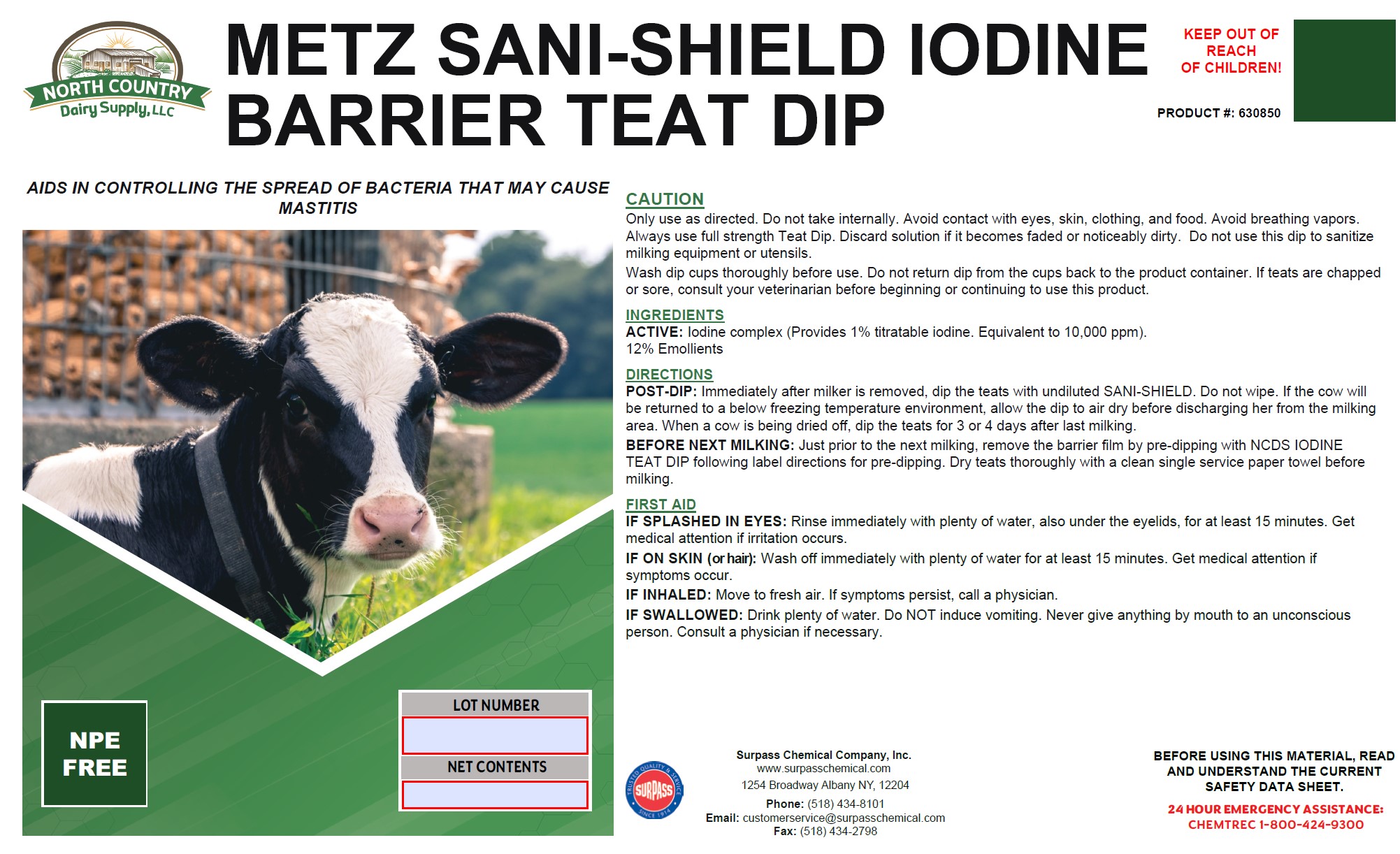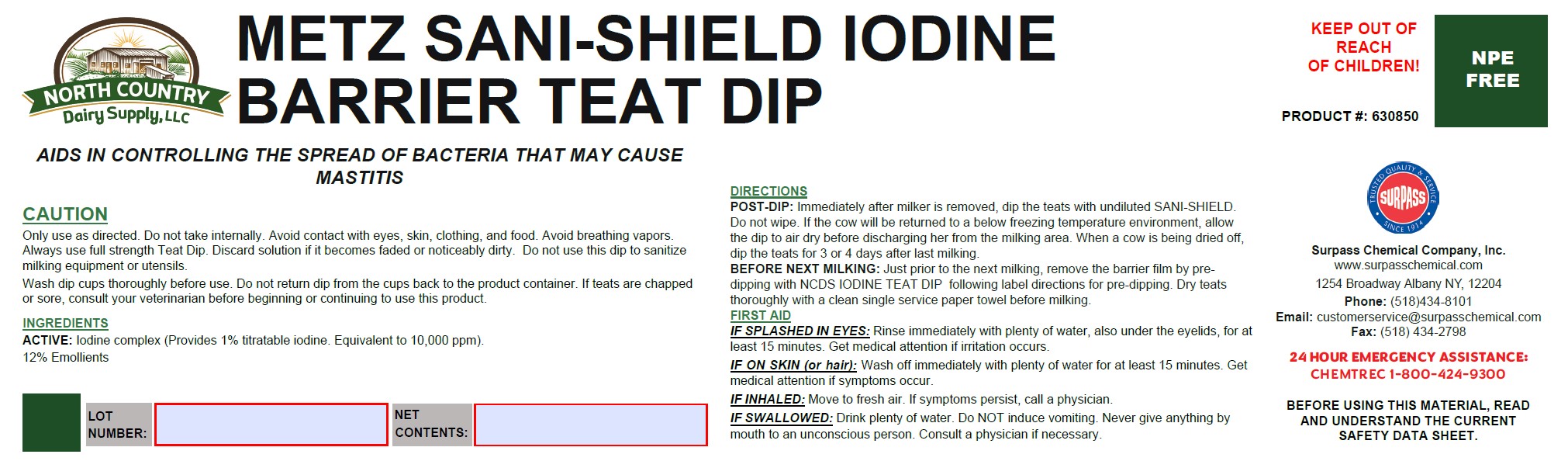 DRUG LABEL: Metz Sani-Shield Iodine Barrier Teat Dip
NDC: 86067-0122 | Form: SOLUTION
Manufacturer: Surpass Chemical Company, Inc.
Category: animal | Type: OTC ANIMAL DRUG LABEL
Date: 20240506

ACTIVE INGREDIENTS: iodine 0.04724 kg/1 kg
INACTIVE INGREDIENTS: WATER 0.87076 kg/1 kg; C9-11 PARETH-8 0.02 kg/1 kg; ALOE VERA FLOWER 0.0005 kg/1 kg; GLYCERIN 0.05 kg/1 kg; SODIUM BICARBONATE 0.0025 kg/1 kg; XANTHAN GUM 0.003 kg/1 kg; BUTYLENE GLYCOL 0.006 kg/1 kg

Metz Sani-Shield Iodine Barrier Teat Dip

DESCRIPTION

METZ SANI-SHIELD

AIDS IN CONTROLLING THE SPREAD OF BACTERIA THAT MAY CAUSE MASTITIS PRODUCT #: 630850

DIRECTIONS:
POST-DIP: Immediately after milker is removed, dip the teats with undiluted SANI-SHIELD. Do not wipe. If the cow will be
returned to a below freezing temperature environment, allow the dip to air dry before discharging her from the milking area.
When a cow is being dried off, dip the teats for 3 or 4 days after last milking.
BEFORE THE NEXT MILKING: Just prior to the next milking, remove the barrier film by pre-dipping with NCDS IODINE
TEAT DIP following label directions for pre-dipping. Dry teats thoroughly with a clean single service paper towel before
milking.

GENERAL PRECAUTIONS

CAUTION:
Only use as directed. Do not take internally. Avoid contact with eyes, skin, clothing, and food. Avoid breathing vapors.
Always use full strength Teat Dip. Discard solution if it becomes faded or noticeably dirty. Do not use this dip to sanitize
milking equipment or utensils.
Wash dip cups thoroughly before use. Do not return dip from the cups back to the product container. If teats are chapped or
sore, consult your veterinarian before beginning or continuing to use this product.

PRECAUTIONS

PRECAUTIONARY STATEMENTS
Prevention: Do not breathe dust/fume/gas/mist/vapors/spray Wash face, hands and any exposed skin thoroughly after
handling Do not eat, drink or smoke when using this product
Response: Get medical advice/attention if you feel unwell
Disposal: Dispose of contents/container to an approved waste disposal plant

OTHER SAFETY INFORMATION

FIRST AID:
IF SPLASHED IN EYES: Rinse immediately with plenty of water, also under the eyelids, for at least 15 minutes. Get
medical attention if irritation occurs.
IF ON SKIN (or hair): Wash off immediately with plenty of water for at least 15 minutes. Get medical attention if
symptoms occur.
IF INHALED: Move to fresh air. If symptoms persist, call a physician.
IF SWALLOWED: Drink plenty of water. Do NOT induce vomiting. Never give anything by mouth to an unconscious
person. Consult a physician if necessary.

ACTIVE INGREDIENT

INGREDIENTS:
ACTIVE: Iodine complex (Provides 1% titratable iodine. Equivalent to 10,000 ppm).

12% Emollients

KEEP OUT OF REACH OF CHILDREN!

Surpass Chemical Company, Inc. Phone: (518) 434-8101 24 HOUR EMERGENCY ASSISTANCE:
www.surpasschemical.com Fax: (518) 434-2798 CHEMTREC 1-800-424-9300
1254 Broadway Albany NY, 12204 Email: customerservice@surpasschemical.com KEEP OUT OF REACH OF CHILDREN!

BEFORE USING THIS MATERIAL, READ AND
UNDERSTAND THE CURRENT SAFETY DATA SHEET.